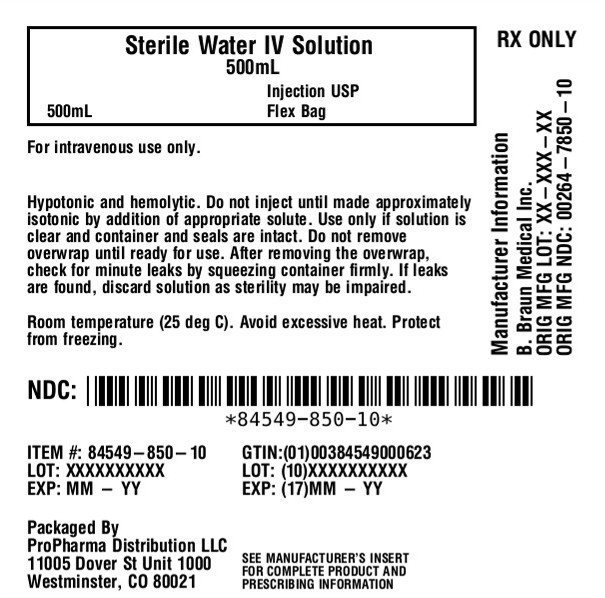 DRUG LABEL: Sterile Water
NDC: 84549-850 | Form: INJECTION
Manufacturer: ProPharma Distribution
Category: prescription | Type: HUMAN PRESCRIPTION DRUG LABEL
Date: 20250919

ACTIVE INGREDIENTS: WATER 1 mL/1 mL

Sterile Water for Injection USP

Warning: Hypotonic and hemolytic.
Do not inject until made approximately isotonic by addition of appropriate solute.

DESCRIPTION

Sterile Water for Injection USP is a clear, colorless, odorless liquid. It is sterile, hypotonic, nonpyrogenic, and contains no bacteriostatic or antimicrobial agents. Sterile Water for Injection USP is a diluent or solvent suitable for intravascular injection after first having been made approximately isotonic by the addition of suitable solute.

pH: 5.5 (5.0–7.0)

Not made with natural rubber latex, PVC or DEHP.

The plastic container is made from a multilayered film specifically developed for parenteral drugs. It contains no plasticizers and exhibits virtually no leachables. The solution contact layer is a rubberized copolymer of ethylene and propylene. The container is nontoxic and biologically inert. The container-solution unit is a closed system and is not dependent upon entry of external air during administration. The container is overwrapped to provide protection from the physical environment and to provide an additional moisture barrier when necessary.

Addition of medication should be accomplished using complete aseptic technique.

The closure system has two ports; the one for the administration set has a tamper evident plastic protector and the other is a medication addition site. Refer to the Directions for Use of the container.

CLINICAL PHARMACOLOGY

Sterile Water for Injection USP is used as a diluent or solvent for other parenteral drugs. As such, Sterile Water for Injection USP contributes to the water for hydration when provided in parenteral drug and fluid therapy, after the introduction of suitable additives and/or mixture with suitable solutes to approximate isotonicity.

INDICATIONS AND USAGE

Sterile Water for Injection USP is indicated for use in adults and pediatric patients as a diluent or solvent in the aseptic preparation of parenteral solutions or as a vehicle for drug administration.

CONTRAINDICATIONS

None known.

WARNINGS

Hypotonic and hemolytic.Do not inject until made approximately isotonic by addition of an appropriate solute, due to the possibility of hemolysis.

The administration of intravenous solutions can cause fluid and/or solute overload resulting in dilution of serum electrolyte concentrations, overhydration, congested states or pulmonary edema. The risk of dilutional states is inversely proportional to the electrolyte concentration.

WARNING: This product contains aluminum that may be toxic. Aluminum may reach toxic levels with prolonged parenteral administration if kidney function is impaired. Premature neonates are particularly at risk because their kidneys are immature, and they require large amounts of calcium and phosphate solutions, which contain aluminum.

Research indicates that patients with impaired kidney function, including premature neonates, who receive parenteral levels of aluminum at greater than 4 to 5 mcg/kg/day accumulate aluminum at levels associated with central nervous system and bone toxicity. Tissue loading may occur at even lower rates of administration.

PRECAUTIONS

General

To minimize the risk of possible incompatibilities arising from the mixing of additives that may be prescribed, the final infusate should be inspected for cloudiness or precipitation immediately after mixing, prior to administration and periodically during administration.

Do not use plastic containers in series connection.

If administration is controlled by a pumping device, care must be taken to discontinue pumping action before the container runs dry or air embolism may result. If administration is not controlled by a pumping device, refrain from applying excessive pressure (>300mmHg) causing distortion to the container such as wringing or twisting. Such handling could result in breakage of the container.

This solution is intended for intravenous administration using sterile equipment. It is recommended that intravenous administration apparatus be replaced at least once every 24 hours.

Use only if solution is clear and container and seals are intact.

The drug product contains no more than 25 mcg/L of aluminum.

Carcinogenesis, Mutagenesis, Impairment of Fertility

Refer to the package insert of the solute used.

Usage in Pregnancy

Refer to the package insert of the solute used.

Nursing Mothers

Refer to the package insert of the solute used.

Pediatric Use

Refer to the package insert of the solute used. See WARNINGSsection regarding aluminum.

Geriatric Use

Refer to the package insert of the solute used. See WARNINGSsection regarding aluminum.

ADVERSE REACTIONS

Refer to the package insert of the solute used.

Reactions which may occur because of the solution or the technique of administration include febrile response, infection at the site of injection, venous thrombosis or phlebitis extending from the site of injection, extravasation and hypervolemia.

The physician should also be alert to the possibility of adverse reactions to drug additives. Prescribing information for drug additives to be administered in this manner should be consulted.

If an adverse reaction does occur, discontinue the infusion, evaluate the patient, institute appropriate therapeutic countermeasures and save the remainder of the fluid for examination if deemed necessary.

OVERDOSAGE

Overdosage (hypotonic expansion) is a function of an increase in fluid intake over fluid output, and occurs when the increase in the volume of body fluids is due to water alone. Overdosage may occur in patients who receive large quantities of electrolyte-free water to replace abnormal excessive fluid losses, in patients whose renal tolerance to water loads is exceeded, or in patients who retain water postoperatively in response to stress.

Manifestations of water intoxication are behavioral changes (confusion, apathy, disorientation and attendant hyponatremia), central nervous system disturbances (weakness, muscle twitching, headaches, nausea, vomiting, convulsions) and weight gain.

Treatment consists of withholding fluids until excessive water is excreted. In severe hyponatremia it may be necessary to cautiously administer hypertonic saline to increase extracellular osmotic pressure and excretion of excess water by the kidneys.

DOSAGE AND ADMINISTRATION

This solution is for intravenous use only. Do not inject until made approximately isotonic by addition of appropriate solute.

The dosage and administration of Sterile Water for Injection USP is dependent upon the recommended dosage and administration of the solute used. Fluid administration should be based on calculated maintenance or replacement fluid requirements for each patient.

Some additives may be incompatible. Consult with pharmacist. When introducing additives, use aseptic techniques. Mix thoroughly. Do not store.

Parenteral drug products should be inspected visually for particulate matter and discoloration prior to administration, whenever solution and container permit.

HOW SUPPLIED

Sterile Water for Injection USP is supplied sterile and nonpyrogenic in EXCEL®Containers.

NDC

Size

Sterile Water for Injection USP

84549-850-10

500 mL

STORAGE AND HANDLING

Exposure of pharmaceutical products to heat should be minimized. Avoid excessive heat. Protect from freezing. It is recommended that the product be stored at room temperature (25°C); however, brief exposure up to 40°C does not adversely affect the product.

Storage in automated dispensing machines: Brief exposure up to 2 weeks to ultraviolet or fluorescent light does not adversely affect the product labeling legibility; prolonged exposure can cause fading of the red label. Rotate stock frequently.

Rx only

EXCEL is a registered trademark of B. Braun Medical Inc.

Directions for Use of EXCEL® Container

Warning: Hypotonic and hemolytic.
Do not inject until made approximately isotonic by addition of appropriate solute.

Caution:Do not use plastic containers in series connection.

To Open

Tear overwrap down at notch and remove solution container. Check for minute leaks by squeezing solution container firmly. If leaks are found, discard solution as sterility may be impaired. If supplemental medication is desired, follow directions below before preparing for administration.

NOTE: Before use, perform the following checks:

Inspect each container. Read the label. Ensure solution is the one ordered and is within the expiration date.

Invert container and carefully inspect the solution in good light for cloudiness, haze, or particulate matter. Any container which is suspect should not be used.

Use only if solution is clear and container and seals are intact.

Preparation for Administration

1. Remove plastic protector from sterile set port at bottom of container.
2. Attach administration set. Refer to complete directions accompanying set.

To Add Medication

Warning:Some additives may be incompatible.

To Add Medication Before Solution Administration

1. Prepare medication site.
2. Using syringe with 18–22 gauge needle, puncture medication port and inner diaphragm and inject.
3. Squeeze and tap ports while ports are upright and mix solution and medication thoroughly.

To Add Medication During Solution Administration

1. Close clamp on the set.
2. Prepare medication site.
3. Using syringe with 18–22 gauge needle of appropriate length (at least 5/8 inch), puncture resealable medication port and inner diaphragm and inject.
4. Remove container from IV pole and/or turn to an upright position.
5. Evacuate both ports by tapping and squeezing them while container is in the upright position.
6. Mix solution and medication thoroughly.
7. Return container to in use position and continue administration.

B. Braun Medical Inc.
Bethlehem, PA 18018-3524 USA
1-800-227-2862
www.bbraun.com